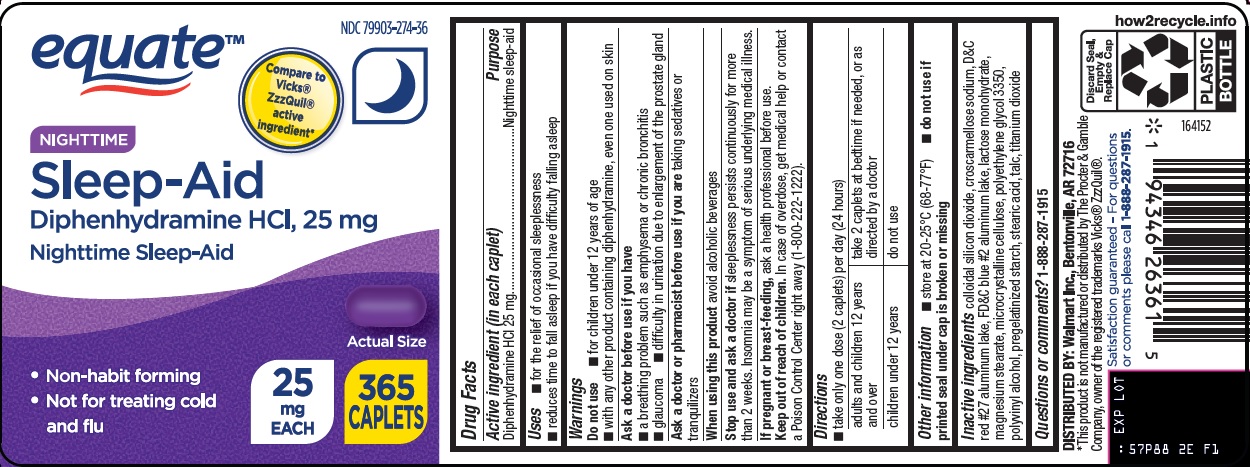 DRUG LABEL: equate nighttime sleep aid
NDC: 79903-274 | Form: TABLET, FILM COATED
Manufacturer: WALMART INC.
Category: otc | Type: HUMAN OTC DRUG LABEL
Date: 20241217

ACTIVE INGREDIENTS: DIPHENHYDRAMINE HYDROCHLORIDE 25 mg/1 1
INACTIVE INGREDIENTS: SILICON DIOXIDE; CROSCARMELLOSE SODIUM; D&C RED NO. 27 ALUMINUM LAKE; FD&C BLUE NO. 2 ALUMINUM LAKE; LACTOSE MONOHYDRATE; MAGNESIUM STEARATE; MICROCRYSTALLINE CELLULOSE; POLYETHYLENE GLYCOL 3350; POLYVINYL ALCOHOL, UNSPECIFIED; STEARIC ACID; TALC; TITANIUM DIOXIDE

Wal-Mart Nighttime Sleep-Aid Drug Facts

Active ingredient (in each caplet)

Diphenhydramine HCl 25 mg

Purpose

Nighttime sleep-aid

Uses

- for the relief of occasional sleeplessness
- reduces time to fall asleep if you have difficulty falling asleep

Warnings

Do not use

- for children under 12 years of age
- with any other product containing diphenhydramine, even one used on skin

Ask a doctor before use if you have

- a breathing problem such as emphysema or chronic bronchitis
- glaucoma
- difficulty in urination due to enlargement of the prostate gland

Ask a doctor or pharmacist before use if you are

taking sedatives or tranquilizers

When using this product

avoid alcoholic beverages

Stop use and ask a doctor if

sleeplessness persists continuously for more than 2 weeks. Insomnia may be a symptom of serious underlying medical illness.

If pregnant or breast-feeding,

ask a health professional before use.

Keep out of reach of children.

In case of overdose, get medical help or contact a Poison Control Center right away (1-800-222-1222).

Directions

- take only one dose (2 caplets) per day (24 hours)

adults and children 12 years and over | take 2 caplets at bedtime if needed, or as directed by a doctor
children under 12 years | do not use

Other information

- store at 20-25°C (68-77°F)
- do not use if printed seal under cap is broken or missing

Inactive ingredients

colloidal silicon dioxide, croscarmellose sodium, D&C red #27 aluminum lake, FD&C blue #2 aluminum lake, lactose monohydrate, magnesium stearate, microcrystalline cellulose, polyethylene glycol 3350, polyvinyl alcohol, pregelatinized starch, stearic acid, talc, titanium dioxide

Questions or comments?

1-888-287-1915

Principal Display Panel

equate™

Compare to Vicks® ZzzQuil® active ingredient

NIGHTTIME

Sleep-Aid

Diphenhydramine HCl, 25 mg

Nighttime Sleep-Aid

Actual Size

• Non-habit forming

• Not for treating cold and flu

25 mg EACH

365 CAPLETS